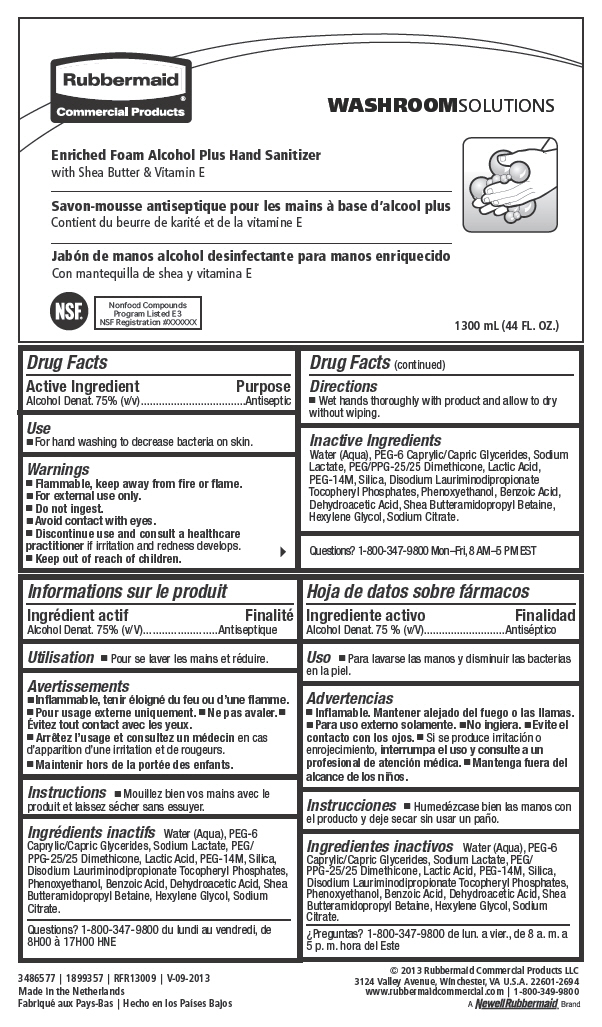 DRUG LABEL: Foam Hand Sanitizer
NDC: 65321-024 | Form: LIQUID
Manufacturer: Rubbermaid Commercial Products LLC
Category: otc | Type: HUMAN OTC DRUG LABEL
Date: 20240709

ACTIVE INGREDIENTS: ALCOHOL 75 mL/100 mL
INACTIVE INGREDIENTS: WATER; SODIUM LACTATE; LACTIC ACID, UNSPECIFIED FORM

TC® ENRICHEDFOAM™
Alcohol Plus Hand Sanitizer

Drug Facts

Active Ingredient

Alcohol 75% (v/v)

Purpose

Antiseptic

Use

- For hand washing to decrease bacteria on skin.

Warnings

DO NOT USE

- Flammable, keep away from fire or flame.
- For external use only.
- Do not ingest.
- Avoid contact with eyes.

STOP USE

- Discontinue use and consult a healthcare practitioner if irritation and redness develops.

- Keep out of reach of children.

Directions

- Wet hands thoroughly with product and allow to dry without wiping.

Inactive Ingredients

Water (Aqua), PEG-6 Caprilic/Capric Glycerides, Shea Butteramidopropyl Betaine, Disodium Lauriminodipropionate Tocopheryl Phosphates, Sodium Lactate, PEG/PPG-25/25 Dimethicone, Lactic Acid, PEG-14M

Questions?

1-800-347-9800 Mon–Fri, 8 AM–5 PM EST

PRINCIPAL DISPLAY PANEL - 1300 mL Bag Label

Rubbermaid®
Commercial Products

WASHROOMSOLUTIONS

Enriched Foam Alcohol Plus Hand Sanitizer
with Shea Butter & Vitamin E

NSF®

Nonfood Compounds
Program Listed E3
NSF Registration #XXXXXX

1300 mL (44 FL. OZ.)